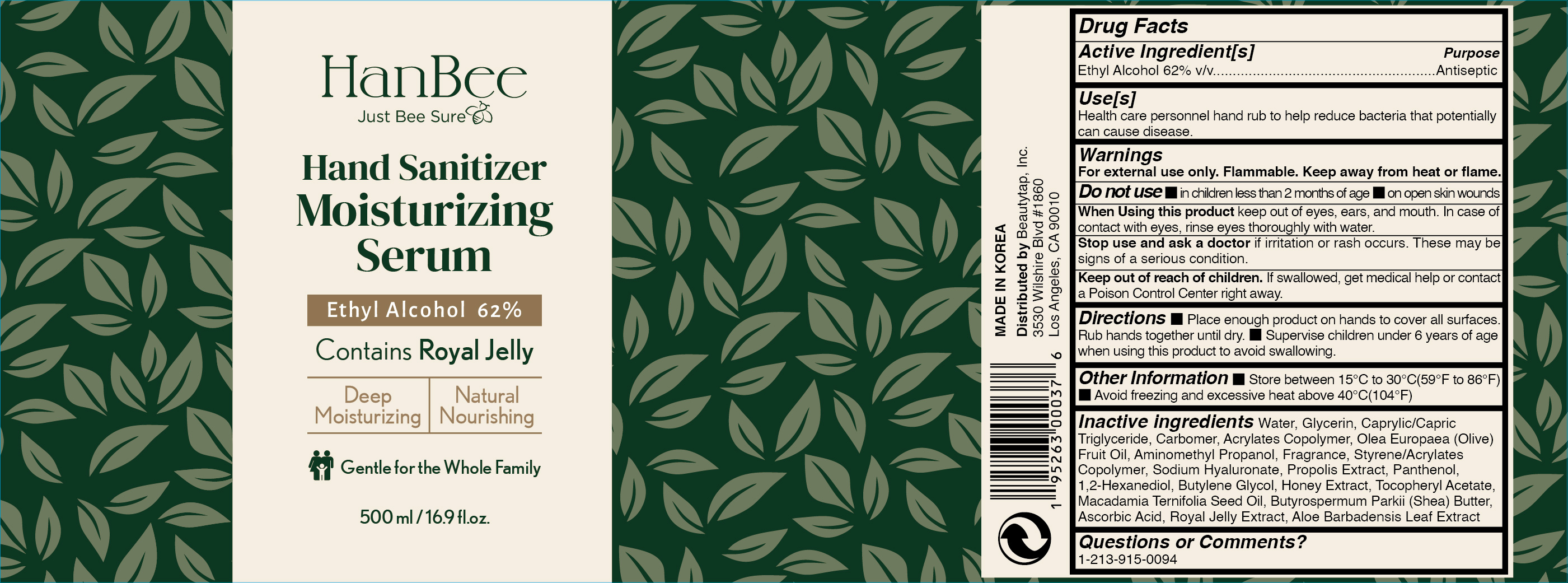 DRUG LABEL: Hand Sanitizer
NDC: 73862-224 | Form: LOTION
Manufacturer: E.CIS COSMETIC.Co.,Ltd
Category: otc | Type: HUMAN OTC DRUG LABEL
Date: 20210303

ACTIVE INGREDIENTS: ALCOHOL 62 mL/100 mL
INACTIVE INGREDIENTS: GLYCERIN; WATER; OLIVE OIL; CARBOMER 940; BUTYLENE GLYCOL; ROYAL JELLY; ALOE VERA LEAF; AMINOMETHYLPROPANOL; STYRENE/ACRYLAMIDE COPOLYMER (MW 500000); HYALURONATE SODIUM; 1,2-HEXANEDIOL; HONEY; MACADAMIA OIL; ALPHA-TOCOPHEROL ACETATE; BUTYL ACRYLATE/METHYL METHACRYLATE/METHACRYLIC ACID COPOLYMER (18000 MW); ASCORBIC ACID; SHEA BUTTER; PROPOLIS WAX; PANTHENOL; MEDIUM-CHAIN TRIGLYCERIDES

HANBEE Hand Sanitizer Moisturizing Serum 62% 500ml

Active Ingredient(s)

Ethyl Alcohol 62% v/v. Purpose: Antiseptic

Purpose

Antiseptic, Hand Sanitizer

Use

Health care personnel hand rub to help reduce bacteria that potentially can cause disease.

Warnings

For external use only. Flammable. Keep away from heat or flame

Do not use

- in children less than 2 months of age
- on open skin wounds

When using this product keep out of eyes, ears, and mouth. In case of contact with eyes, rinse eyes thoroughly with water.

Stop use and ask a doctor if irritation or rash occurs. These may be signs of a serious condition.

Keep out of reach of children. If swallowed, get medical help or contact a Poison Control Center right away.

Directions

Place enough product on hands to cover all surfaces. Rub hands together until dry.
Supervise children under 6 years of age when using this product to avoid swallowing.

Other information

- Store between 15-30C (59-86F)
- Avoid freezing and excessive heat above 40C (104F)

Inactive ingredients

Water, Cetyl Alcohol, Glycerin, Caprylic/Capric Triglyceride, Acrylates Copolymer, Olea Europaea (Olive) Fruit Oil, Carbomer, Aminomethyl Propanol, Fragrance, Styrene/Acrylates Copolymer, Sodium Hyaluronate, Propolis Extract, Panthenol, 1,2-Hexanediol, Butylene Glycol, Honey Extract, Macadamia Ternifolia Seed Oil, Butyrospermum Parkii (Shea) Butter, Ascorbic Acid, Tocopheryl Acetate, Royal Jelly Extract, Aloe Barbadensis Leaf Extract

Package Label - Principal Display Panel

HanBee
Just Bee Sure
Hand Sanitizer Moisturizing Serum
Ethyl Alcohol 62%
Contains Royal Jelly
Deep Moisturizing Natural Nourishing
Gentle for the Whole Family
500 mL (16.9 fl. oz.)